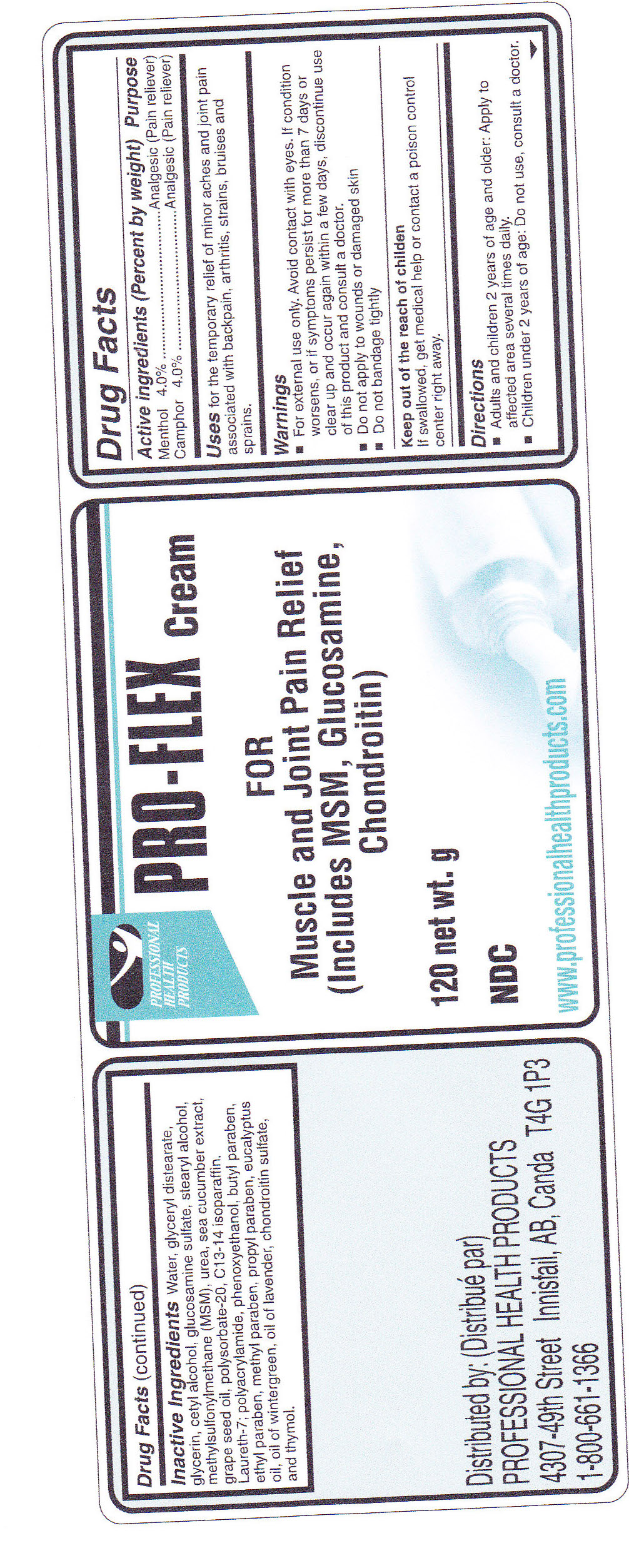 DRUG LABEL: Pro-Flex
								
NDC: 49795-227 | Form: CREAM
Manufacturer: Nutri-Dyn Products Ltd. dba Professional Health Products
Category: otc | Type: HUMAN OTC DRUG LABEL
Date: 20110620

ACTIVE INGREDIENTS: CAMPHOR (NATURAL) 4 g/100 g; Menthol 4 g/100 g
INACTIVE INGREDIENTS: Water; Cetyl alcohol; Glycol stearate; Dimethyl sulfone; Glycerin; Stearyl alcohol; Glucosamine sulfate; C13-14 Isoparaffin; Polysorbate 20; Urea; Phenoxyethanol; Caprylyl glycol; Sorbic acid; Eucalyptus oil; Methyl salicylate; Vitamin E; LAVANDULA ANGUSTIFOLIA FLOWER; Thymol; Chondroitin sulfate (bovine); CUCUMARIA SEA CUCUMBER; Grape seed oil

PRO-FLEX Cream

Active Ingredients (Percent by weight) Purpose

Menthol 4.0% ............................Analgesic (Pain reliever)

Camphor 4.0% ...........................Analgesic (Pain reliever)

INDICATIONS AND USAGE

Uses for the temporary relief of minor aches and joint pain associated with backpain, arthritis, strains, bruises and sprains.

Warnings

- For external use only. Avoid contact with eyes. If condition worsens, or if symptoms persist for more than 7 days or clear up and occur again within a few days,discontinue use of this product and consult a doctor.
- Do not apply to wounds or damaged skin
- Do not bandage tightly

Keep out of the reach of children

If swallowed, get medical help or contact a poison control center right away.

Directions

- Adults and children 2 years of age and older: Apply to affected area several times daily.
- Children under 2 years of age: Do not use, consult a doctor.

INACTIVE INGREDIENT

C13-14 isoparaffin, caprylyl glycol, cetyl alcohol, chondroitin sulfate, denatured alcohol, eucalyptus oil, glucosamine sulfate, glycerin, grape seed oil, laureth-7, methylsulfonylmethane (MSM), oil of lavender, oil of wintergreen, phenoxyethanol, polyacrylamide, polysorbate-20, sea cucumber extract, sorbic, acid, stearyl alcohol, thymol, urea, vitamin E, water

REFERENCES

Distributed by:

PROFESSIONAL HEALTH PRODUCTS

4307-49th Street Innisfail, AB CANADA T4G 1P3

1-403-227-3926

PURPOSE

Pain Reliever

PACKAGE LABEL

Professional Health Products

PRO-FLEX Cream

FOR

Muscle Pain/Joint Relief

(Includes MSM, Glucosamine, Chondroitin)

120 net wt. g

www.professionalhealthproducts.com